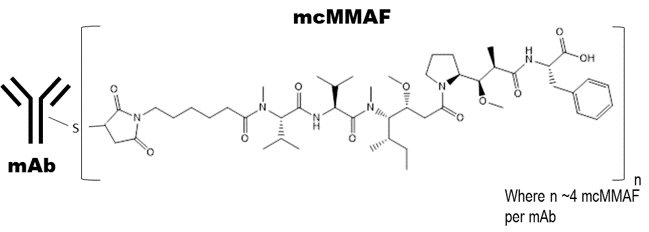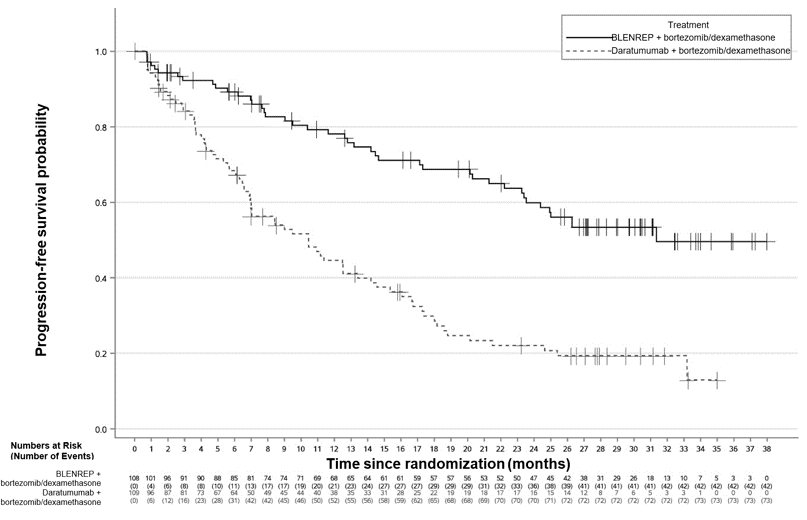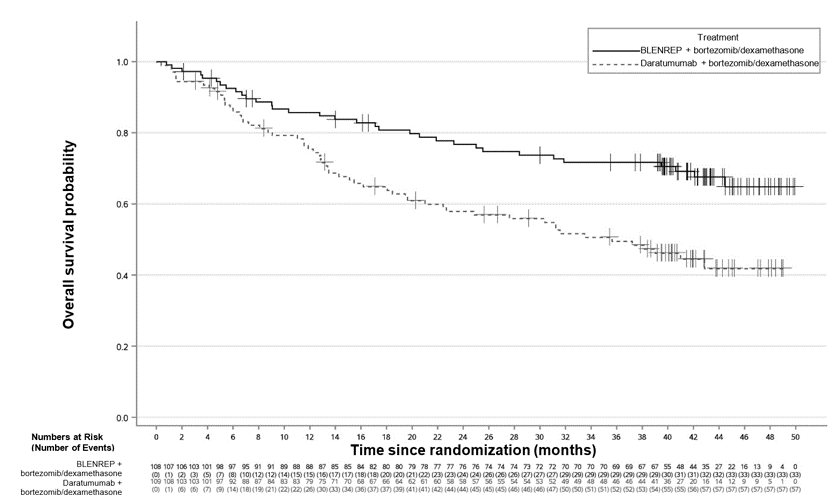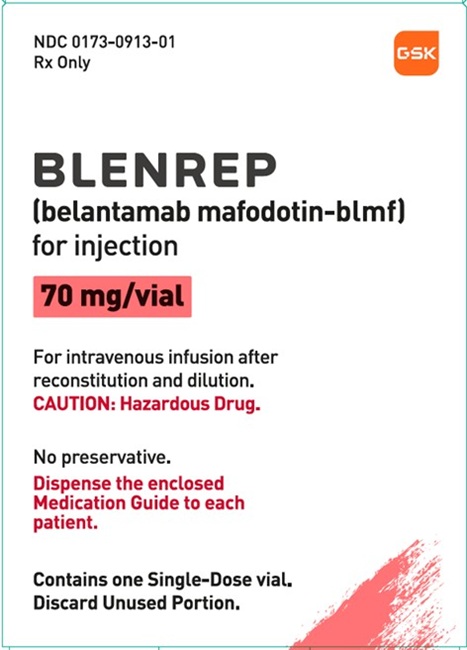 DRUG LABEL: Blenrep
NDC: 0173-0913 | Form: INJECTION, POWDER, FOR SOLUTION
Manufacturer: GlaxoSmithKline LLC
Category: prescription | Type: HUMAN PRESCRIPTION DRUG LABEL
Date: 20251023

ACTIVE INGREDIENTS: BELANTAMAB MAFODOTIN 50 mg/1 mL
INACTIVE INGREDIENTS: CITRIC ACID MONOHYDRATE; EDETATE DISODIUM; POLYSORBATE 80; SODIUM CITRATE, UNSPECIFIED FORM; TREHALOSE

HIGHLIGHTS OF PRESCRIBING INFORMATION

These highlights do not include all the information needed to use BLENREP safely and effectively. See full prescribing information for BLENREP.
BLENREP (belantamab mafodotin-blmf) for injection, for intravenous use
Initial U.S. Approval: 2020

WARNING: OCULAR TOXICITY

See full prescribing information for complete boxed warning.

- BLENREP causes changes in the corneal epithelium resulting in changes in vision, including severe visual impairment, and symptoms such as blurred vision and dry eyes. In the clinical study, corneal ulcers, including cases with infection, also occurred. (5.1)
- Conduct ophthalmic exams at baseline, before each dose, promptly for new or worsening symptoms, and as clinically indicated. In the clinical study, 83% of patients required a dosage modification due to ocular toxicity. Withhold BLENREP until improvement and resume or permanently discontinue, based on severity. (2.3, 5.1)
- BLENREP is available only through a restricted program, called the BLENREP Risk Evaluation and Mitigation Strategy (REMS). (5.2)

1 INDICATIONS AND USAGE

BLENREP, a B‑cell maturation antigen (BCMA)‑directed antibody and microtubule inhibitor conjugate, is indicated in combination with bortezomib and dexamethasone for the treatment of adult patients with relapsed or refractory multiple myeloma who have received at least two prior lines of therapy, including a proteasome inhibitor and an immunomodulatory agent. (1)

2 DOSAGE AND ADMINISTRATION

- The recommended dosage of BLENREP, in combination with bortezomib and dexamethasone, is 2.5 mg/kg as an intravenous infusion over 30 minutes once every 3 weeks for 8 cycles, followed by BLENREP 2.5 mg/kg every 3 weeks as a single agent. (2.2)
- See Full Prescribing Information for instructions on preparation and administration. (2.4)

3 DOSAGE FORMS AND STRENGTHS

For injection: 70 mg as a lyophilized powder in a single‑dose vial for reconstitution and further dilution. (3)

4 CONTRAINDICATIONS

None. (4)

5 WARNINGS AND PRECAUTIONS

- Thrombocytopenia: Monitor complete blood counts at baseline and periodically during treatment. Withhold or reduce the dosage based on severity. (2.3, 5.3)
- Embryo‑fetal Toxicity: Can cause fetal harm. Advise patients of the potential risk to fetus and to use effective contraception. (5.4, 8.1, 8.3)

6 ADVERSE REACTIONS

The most common adverse reactions (≥20%) with BLENREP in combination with bortezomib and dexamethasone are reduction in best-corrected visual acuity (BCVA), corneal exam findings, blurred vision, dry eye, photophobia, foreign body sensation in eyes, eye irritation, upper respiratory tract infection, hepatotoxicity, eye pain, diarrhea, fatigue, pneumonia, cataract, and COVID-19. The most common Grade 3 or 4 (≥10%) laboratory abnormalities are decreased platelets, decreased lymphocytes, decreased neutrophils, increased gamma-glutamyl transferase, decreased white blood cells, and decreased hemoglobin. (6.1)

To report SUSPECTED ADVERSE REACTIONS, contact GlaxoSmithKline at 1-888-825-5249 or FDA at 1-800-FDA-1088 or www.fda.gov/medwatch.

8 USE IN SPECIFIC POPULATIONS

Lactation: Advise not to breastfeed. (8.2)

FULL PRESCRIBING INFORMATION

WARNING: OCULAR TOXICITY

- BLENREP causes changes in the corneal epithelium resulting in changes in vision, including severe visual impairment, and symptoms such as blurred vision and dry eyes. In the clinical study, corneal ulcers, including cases with infection, also occurred [see Warnings and Precautions (5.1)].
- Conduct ophthalmic exams at baseline, before each dose, promptly for new or worsening symptoms, and as clinically indicated. In the clinical study, 83% of patients required a dosage modification due to ocular toxicity. Withhold BLENREP until improvement and resume or permanently discontinue, based on severity [see Dosage and Administration (2.3), Warnings and Precautions (5.1)].
- Because of the risk of ocular toxicity, BLENREP is available only through a restricted program called the BLENREP Risk Evaluation and Mitigation Strategy (REMS) [see Warnings and Precautions (5.2)].

1 INDICATIONS AND USAGE

BLENREP is indicated in combination with bortezomib and dexamethasone for the treatment of adult patients with relapsed or refractory multiple myeloma who have received at least two prior lines of therapy, including a proteasome inhibitor and an immunomodulatory agent.

2 DOSAGE AND ADMINISTRATION

2.1 Important Safety Information

Ophthalmic exams, including slit lamp exam and assessment of best‑corrected visual acuity (BCVA), should be conducted by an eye care professional, such as an ophthalmologist or optometrist. Conduct ophthalmic exams at baseline, before each dose of BLENREP, promptly for new or worsening symptoms, and as clinically indicated [see Warnings and Precautions (5.1)].

Counsel patients to promptly inform their healthcare provider of any ocular symptoms. Advise patients to use preservative‑free artificial tears at least 4 times a day starting with the first infusion and continuing until end of treatment, and to avoid wearing contact lenses for the duration of therapy. Bandage contact lenses may be used under the direction of an eye care professional [see Warnings and Precautions (5.1)].

2.2 Recommended Dosage

The recommended dosage for BLENREP is 2.5 mg/kg of actual body weight once every 3 weeks in combination with bortezomib and dexamethasone (BVd) for the first 8 cycles, followed by BLENREP 2.5 mg/kg of actual body weight once every 3 weeks as a single agent until disease progression or unacceptable toxicity.

For dosing instructions of agents administered in combination with BLENREP, see Clinical Studies (14) and respective Prescribing Information, as appropriate.

BLENREP is administered as an intravenous infusion over approximately 30 minutes.

2.3 Dosage Modifications for Adverse Reactions

In the BVd arm of the clinical study, 98% of patients required a dosage modification for any component of treatment for an adverse reaction, including 87% who required a dosage modification of BLENREP [see Clinical Studies (14)]. Eighty-three percent of patients required a dosage modification of BLENREP for ocular toxicity based on ophthalmic exam findings or other ocular adverse reactions as defined by the Common Terminology Criteria for Adverse Events (CTCAE) [see Adverse Reactions (6.1)]. There were high rates of dosage modifications in early treatment cycles. By Cycle 3, 53% of patients had a dosage interruption or reduction, 7% had discontinued treatment, and only 40% received the planned dose of BLENREP.

The recommended dosage modifications for ocular toxicity based on ophthalmic exam findings are provided in Tables 1 and 2. Ophthalmic exam findings include both corneal exam findings and change in BCVA as assessed by an eye care professional. The overall grade of ophthalmic exam findings is based on the worst finding in the worst affected eye, based on either corneal exam finding or a change in BCVA. Corneal exam findings may or may not be accompanied by changes in BCVA or ocular symptoms.

- Do not re‑escalate the dose of BLENREP after a dosage reduction is made for ocular toxicity based on ophthalmic exam findings.
- In the clinical study, 67% of patients required a dosage interruption of BLENREP for ocular toxicity that lasted longer than 3 weeks (time between doses, median: 5.7 weeks [range: 3 to 31 weeks]).

The recommended dosage modifications for other adverse reactions, including dosage modifications for ocular adverse reactions based on the CTCAE, are provided in Table 3.

Table 1. Recommended Dosage Reductions of BLENREP for Adverse Reactions
 | BLENREP
Reduced Dosage Level 1 | 1.9 mg/kg every 3 weeks
Reduced Dosage Level 2a | 1.9 mg/kg every 8 weeks
a Reduced Dosage Level 2 is specific to dosage reductions due to ocular toxicity based on ophthalmic exam findings.

Table 2. Recommended Dosage Modifications for Ocular Toxicity Based on Ophthalmic Exam Findingsa
Severity | Ophthalmic Exam Findings; [see Warnings and Precautions (5.1)] | Recommended Dosage Modification
Grade 1 | Corneal Exam Findings:; Mild superficial punctate keratopathya; and/or; Change in BCVA:; Decline from baseline of 1 line on Snellen Equivalent BCVA | Continue treatment at current dosage.
Grade 2 | Corneal Exam Findings:; Moderate superficial punctate keratopathy, patchy microcyst‑like depositsb, peripheral sub‑epithelial haze, or a new peripheral stromal opacity; and/or; Change in BCVA:; Decline from baseline of 2 lines on Snellen Equivalent BCVA and not worse than 20/200 | Withhold BLENREP until improvement in both corneal exam findings and change in BCVA to Grade 1 or less. Resume treatment at Reduced Dosage Level 1 as per Table 1. If recurrent Grade 2 or 3 ocular toxicity is experienced, resume treatment at Reduced Dosage Level 2.
Grade 3 | Corneal Exam Findings:; Severe superficial punctate keratopathy, diffuse microcyst‑like depositsb involving the central cornea, central sub‑epithelial haze, or a new central stromal opacity; and/or; Change in BCVA:; Decline from baseline of 3 or more lines on Snellen Equivalent BCVA and not worse than 20/200 | Withhold BLENREP until improvement in both corneal exam findings and change in BCVA to Grade 1 or less. Resume treatment at Reduced Dosage Level 1 as per Table 1. If recurrent Grade 2 or 3 ocular toxicity is experienced, resume treatment at Reduced Dosage Level 2.
Grade 4 | Corneal Exam Findings:; Corneal epithelial defect or corneal ulcer, with or without infection; and/or; Change in BCVA:; Decline to Snellen Equivalent BCVA of worse than 20/200 | Consider permanent discontinuation of BLENREP.; If continuing treatment, withhold BLENREP until improvement in both corneal exam findings and change in BCVA to Grade 1 or less. For patients previously on 2.5 mg/kg every 3 weeks, resume treatment at Reduced Dosage Level 1 as per Table 1. For patients previously on 1.9 mg/kg every 3 weeks, resume treatment at Reduced Dosage Level 2.; If recurrent Grade 4 ocular toxicity is experienced, permanently discontinue BLENREP.
BCVA = best‑corrected visual acuity.
a Mild superficial keratopathy (documented worsening from baseline). Refer to Table 3 for recommended dosage modifications for other ocular adverse reactions.
b Microcyst‑like deposits are considered at least a Grade 2 finding. Withhold BLENREP if any microcyst‑like deposits are observed.

Table 3. Recommended Dosage Modifications for Other Adverse Reactionsa
Adverse Reaction | Severity | Recommended Dosage Modification
Thrombocytopenia; [see Warnings and Precautions (5.3)] | Platelet count between 25,000/mcL and 50,000/mcL without bleeding | For patients on 2.5 mg/kg, reduce to Reduced Dosage Level 1 as per Table 1.b For patients on 1.9 mg/kg, continue at same dosage.
Thrombocytopenia; [see Warnings and Precautions (5.3)] | Platelet count between 25,000/mcL and 50,000/mcL with bleeding | Withhold BLENREP until bleeding resolves. For patients previously on 2.5 mg/kg, resume at Reduced Dosage Level 1 as per Table 1. For patients on 1.9 mg/kg, resume at same dosage.
Thrombocytopenia; [see Warnings and Precautions (5.3)] | Platelet count less than 25,000/mcL | Withhold BLENREP until platelet count recovers to 25,000/mcL or higher. For patients previously on 2.5 mg/kg, resume at Reduced Dosage Level 1 as per Table 1. For patients on 1.9 mg/kg, resume at same dosage.
Infusion-related Reactions | Grade 2 | Interrupt infusion and provide supportive care. Once symptoms resolve to Grade 1 or less, resume infusion at 50% of the initial rate prior to the event. Consider premedication for subsequent infusions.
Infusion-related Reactions | Grade 3 | Interrupt infusion and provide supportive care. Once symptoms resolve to Grade 1 or less, resume at 50% of the initial rate prior to the event. Administer premedication for subsequent infusions.
Infusion-related Reactions | Grade 4 | Permanently discontinue BLENREP.; If anaphylactic or life‑threatening infusion reaction, permanently discontinue the infusion and institute appropriate emergency care.
Other Adverse Reactions; [see Adverse Reactions (6.1] | Grade 3 | Withhold BLENREP until adverse reaction improves to Grade 1 or less. For patients previously on 2.5 mg/kg, resume at Reduced Dosage Level 1 as per Table 1. For patients on 1.9 mg/kg, resume at same dosage.
Other Adverse Reactions; [see Adverse Reactions (6.1] | Grade 4 | Consider permanent discontinuation of BLENREP.; If continuing treatment, withhold BLENREP until adverse reaction improves to Grade 1 or less.; For patients previously on 2.5 mg/kg, resume at Reduced Dosage Level 1 as per Table 1. For patients on 1.9 mg/kg, resume at same dosage.
a Adverse reactions were graded according to the Common Terminology Criteria for Adverse Events v5.0.
b Consider reverting to previous dose, if appropriate once platelet count recovers to 50,000/mcL or higher.

2.4 Preparation and Administration

BLENREP is a hazardous drug. Follow applicable special handling and disposal procedures.^1

Calculate the dose (mg), total volume (mL) of solution required, and the number of vials of BLENREP needed based on the patient’s actual body weight. More than one vial may be needed for a full dose.

Reconstitution

- Remove the vial(s) of BLENREP from the refrigerator and allow to stand for approximately 10 minutes to reach room temperature (68°F to 77°F [20°C to 25°C]).
- Reconstitute each 70 mg vial of BLENREP with 1.4 mL of Sterile Water for Injection, USP, to obtain a final concentration of 50 mg/mL. Gently swirl the vial to aid dissolution. Do not shake.
- If the reconstituted solution is not used immediately, store in the original container refrigerated at 36ºF to 46ºF (2ºC to 8ºC) or at room temperature (68°F to 77°F [20°C to 25°C]) for up to 4 hours. Discard if not diluted within 4 hours. Do not freeze.
- Parenteral drug products should be inspected visually for particulate matter and discoloration prior to administration, whenever solution and container permit. The reconstituted solution should be a clear to opalescent, colorless to yellow to brown liquid. Discard if extraneous particulate matter is observed.

Dilution

- Withdraw the calculated volume of BLENREP from the appropriate number of vials and dilute in a 250 mL infusion bag of 0.9% Sodium Chloride Injection, USP, to a final concentration of 0.2 mg/mL to 2 mg/mL. The infusion bag must be made of polyvinylchloride (PVC) or polyolefin (PO).
- Mix the diluted solution by gentle inversion. Do not shake.
- Discard any unused reconstituted solution of BLENREP left in the vial(s).
- If the diluted infusion solution is not used immediately, store refrigerated at 36ºF to 46ºF (2ºC to 8ºC) for up to 24 hours. Do not freeze. Once removed from refrigeration, administer the diluted infusion solution of BLENREP within 6 hours (including infusion time).
- Parenteral drug products should be inspected visually for particulate matter and discoloration prior to administration, whenever solution and container permit. The diluted infusion solution should be clear and colorless. Discard if particulate matter is observed.

Administration

- If refrigerated, allow the diluted infusion solution to equilibrate to room temperature (68ºF to 77ºF [20ºC to 25ºC]) prior to administration. Diluted infusion solution may be kept at room temperature for no more than 6 hours (including infusion time).
- Administer by intravenous infusion over approximately 30 minutes using an infusion set made of PVC or PO.
- Filtration of the diluted solution is not required; however, if the diluted solution is filtered, use a polyethersulfone (PES)-based filter (0.2 micron).

Do not mix or administer BLENREP with other products. The product does not contain a preservative.

3 DOSAGE FORMS AND STRENGTHS

For injection: 70 mg of belantamab mafodotin-blmf as a white to yellow lyophilized powder in a single-dose vial for reconstitution and further dilution.

4 CONTRAINDICATIONS

None.

5 WARNINGS AND PRECAUTIONS

5.1 Ocular Toxicity

BLENREP causes ocular toxicity, defined as changes in the corneal epithelium and changes in BCVA based on ophthalmic exam (including slit lamp exam), or other ocular adverse reactions as defined by the CTCAE [see Adverse Reactions (6.1)].

In DREAMM-7, ocular toxicity occurred in 92% of patients, including Grade 3 or 4 in 77% of patients. The most common ocular toxicities (>25%) were reduction in BCVA (89%) and corneal exam findings (86%) based on ophthalmic exam findings, blurred vision (66%), dry eye (51%), photophobia (47%), foreign body sensation in eyes (44%), eye irritation (43%), and eye pain (33%) [see Adverse Reactions (6.1)].

Ocular toxicity based on ophthalmic exam findings was reported as Grade 2 in 9% of patients, Grade 3 in 56% of patients, and Grade 4 in 21% of patients. The median time to onset of the first Grade 2 to 4 ophthalmic exam findings was 43 days (range: 15 to 611 days). The median duration of all Grade 2 to 4 ophthalmic exam findings was 85 days (range: 5 to 813 days). Patients experienced a median of 3 episodes (range: 1 to 11 episodes) of ocular toxicity based on ophthalmic exam findings. Of the patients with Grade 2 to 4 ophthalmic exam findings, 42% had improvement of the last event to Grade 1 or better; 22% had resolution of the last event based on return to baseline or normal ophthalmic exam findings.

The most commonly reported corneal exam findings included superficial punctate keratopathy, microcyst-like deposits, epithelial changes, and haze. Cases of corneal ulcer, including cases with infection, have been reported and should be managed promptly by an eye care professional [see Adverse Reactions (6.1)].

A reduction in BCVA to 20/50 or worse in at least one eye occurred in 69% of patients, including 29% who experienced a change in BCVA to 20/100 or worse, and 12% who experienced a change in BCVA to 20/200 or worse. Of the patients with reduced BCVA to 20/50 or worse in at least one eye, 61% had resolution of the last event to baseline or better. Of the patients with reduced BCVA to 20/100 or worse, 57% had resolution of the last event. Of the patients with reduced BCVA to 20/200 or worse, 48% had resolution of the last event.

Ophthalmic exams (including slit lamp exam and BCVA assessment) should be conducted by an eye care professional, such as an ophthalmologist or optometrist, at baseline, before each dose of BLENREP, promptly for new or worsening symptoms, and as clinically indicated. Perform baseline exam within 4 weeks prior to the first dose. Perform each follow-up exam within 10 days prior to the next planned dose. All effort should be made to schedule the exam as close to BLENREP dosing as possible. Withhold BLENREP until improvement in both corneal exam findings and change in BCVA to Grade 1 or less and resume at same or reduced dose or permanently discontinue based on severity [see Dosage and Administration (2.1, 2.3)].

Counsel patients to promptly inform their healthcare provider of any ocular symptoms. Counsel patients to use preservative‑free artificial tears at least 4 times a day starting with the first infusion and continuing until the end of treatment, and to avoid wearing contact lenses for the duration of therapy. Bandage contact lenses may be used under the direction of an eye care professional [see Dosage and Administration (2.1)].

Changes in visual acuity may be associated with difficulty for driving and reading. Counsel patients to use caution when driving or operating machinery.

BLENREP is available only through a restricted program under a Risk Evaluation and Mitigation Strategy (REMS) [see Warnings and Precautions (5.2)].

5.2 BLENREP Risk Evaluation and Mitigation Strategy (REMS)

BLENREP is available only through a restricted program called the BLENREP REMS because of the risk of ocular toxicity [see Warnings and Precautions (5.1)].

Notable requirements of the BLENREP REMS include the following:

- Prescribers must be certified in the BLENREP REMS by enrolling and completing training.
- Prescribers must counsel patients receiving BLENREP on the risk of ocular toxicity, the need for monitoring via ophthalmic exams before each dose, and provide patients with the BLENREP REMS Patient Guide.
- Patients must be enrolled in the BLENREP REMS and adhere to monitoring.
- Healthcare settings that dispense BLENREP must be certified in the BLENREP REMS by enrolling and must obtain authorization prior to dispensing.
- Wholesalers and distributors must distribute BLENREP only to certified healthcare settings.

Further information is available at www.BLENREPREMS.com and 1‑855‑690-9572.

5.3 Thrombocytopenia

Thrombocytopenia of any grade occurred in 100% of patients in DREAMM‑7 [see Adverse Reactions (6.1)].

Grade 2 thrombocytopenia occurred in 10% of patients, Grade 3 in 29% of patients, and Grade 4 in 45% of patients. Clinically significant bleeding (Grade ≥2) occurred in 7% of patients with concomitant low platelet levels (Grade 3 or 4).

Monitor complete blood cell counts at baseline and periodically during treatment as clinically indicated. Withhold or reduce the dose of BLENREP based on severity [see Dosage and Administration (2.3)].

5.4 Embryo-fetal Toxicity

Based on its mechanism of action, BLENREP can cause fetal harm when administered to a pregnant woman because it contains a genotoxic compound (the microtubule inhibitor, monomethyl auristatin F [MMAF]) and it targets actively dividing cells.

Advise pregnant women of the potential risk to a fetus. Advise females of reproductive potential to use effective contraception during treatment with BLENREP and for 4 months after the last dose. Advise males with female partners of reproductive potential to use effective contraception during treatment with BLENREP and for 6 months after the last dose [see Use in Specific Populations (8.1, 8.3)].

6 ADVERSE REACTIONS

The following clinically significant adverse reactions are described elsewhere in the labeling:

- Ocular Toxicity [see Warnings and Precautions (5.1)]
- Thrombocytopenia [see Warnings and Precautions (5.3)]

6.1 Clinical Trials Experience

Because clinical trials are conducted under widely varying conditions, adverse reaction rates observed in the clinical trials of a drug cannot be directly compared with rates in the clinical trials of another drug and may not reflect the rates observed in practice.

Relapsed or Refractory Multiple Myeloma in Combination with Bortezomib and Dexamethasone

The safety of BLENREP with bortezomib and dexamethasone (n = 242) compared with daratumumab with bortezomib and dexamethasone (n = 246) was evaluated in DREAMM‑7 in patients with relapsed or refractory multiple myeloma who received at least one prior line of therapy [see Clinical Studies (14)]. Patients received BLENREP 2.5 mg/kg of actual body weight once every 3 weeks in combination with bortezomib and dexamethasone (BVd) for the first 8 cycles, followed by BLENREP as a single agent or daratumumab in combination with bortezomib and dexamethasone (DVd) for the first 8 cycles, followed by daratumumab as a single agent. Among patients who received BLENREP, 69% were exposed for 6 months or longer and 55% were exposed for greater than one year. The safety of BLENREP in combination with bortezomib and dexamethasone in patients who received only one prior line of therapy (n = 125) has not been established.

Serious adverse reactions occurred in 50% of patients who received BVd. Serious adverse reactions in ≥2% of patients included pneumonia (18%), pyrexia (5%), thrombocytopenia (5%), COVID-19 (5%), upper respiratory tract infection (4%), sepsis (4%), second primary malignancy (3%), and anemia (2%). Fatal adverse reactions occurred in 10% of patients who received BVd. Fatal adverse reactions which occurred in >1 patient included pneumonia (4%), sepsis (2%), COVID-19 (1%), respiratory failure (<1%), and intracranial hemorrhage (<1%).

Permanent discontinuation of BLENREP due to an adverse reaction occurred in 17% of patients. Adverse reactions which resulted in permanent discontinuation of BLENREP in ≥3% of patients included ocular toxicity (9%) and pneumonia (4%).

Dosage interruptions of BLENREP due to an adverse reaction occurred in 78% of patients. Adverse reactions which required dosage interruption of BLENREP in ≥3% of patients included ocular toxicity based on ophthalmic exam findings (74%), blurred vision (32%), upper respiratory tract infection (20%), dry eye (14%), photophobia (14%), pneumonia (14%), eye irritation (13%), COVID-19 (12%), foreign body sensation in eyes (12%), eye pain (10%), thrombocytopenia (9%), visual impairment (7%), cataract (5%), diarrhea (4%), and neutropenia (4%).

Dosage reductions of BLENREP due to an adverse reaction occurred in 36% of patients. Adverse reactions which required dosage reductions for BLENREP in ≥3% of patients included ocular toxicity based on ophthalmic exam findings (30%), thrombocytopenia (14%), and blurred vision (10%).

The most common adverse reactions (≥20%) were reduction in BCVA, corneal exam findings, blurred vision, dry eye, photophobia, foreign body sensation in eyes, eye irritation, upper respiratory tract infection, hepatotoxicity, eye pain, diarrhea, fatigue, pneumonia, cataract, and COVID-19. The most common Grade 3 or 4 laboratory abnormalities (≥10%) were decreased platelets, decreased lymphocytes, decreased neutrophils, increased gamma glutamyltransferase, decreased white blood cells, and decreased hemoglobin.

Table 4 summarizes the adverse reactions in DREAMM‑7.

Table 4. Adverse Reactions (≥10%) in Patients with Relapsed or Refractory Multiple Myeloma Who Received BLENREP in DREAMM-7
Adverse Reactiona | BLENREP +; Bortezomib and Dexamethasone; N = 242 |  | Daratumumab +; Bortezomib and Dexamethasone; N = 246
Adverse Reactiona | All Grades; (%) | Grades 3‑4; (%) | All Grades; (%) | Grades 3‑4; (%)
Eye disorders
Reduction in BCVAb | 89 | 57 | 44 | 9
Corneal exam findingsb | 86 | 72 | 19 | 3
Blurred vision | 66 | 22 | 11 | 0.8
Dry eyec | 51 | 7 | 7 | 0
Photophobia | 47 | 2 | 2 | 0
Foreign body sensation in eyesc | 44 | 3 | 4 | 0
Eye irritation | 43 | 5 | 5 | 0
Eye painc | 33 | 0.8 | 4 | 0.4
Cataractc | 24 | 8 | 14 | 3
Visual impairment | 11 | 5 | 2 | 0.4
Gastrointestinal disorders
Diarrhea | 32 | 4 | 31 | 4
Nausea | 16 | 0.8 | 12 | 0
Infections
Upper respiratory tract infectionc,d | 38 | 2 | 36 | 2
Pneumoniac,d | 26 | 16 | 17 | 5
COVID-19d | 24 | 5 | 20 | 2
Hepatobiliary disorders
Hepatotoxicityc | 33 | 14 | 16 | 2
General disorders and administration site conditions
Fatiguec | 26 | 6 | 27 | 4
Pyrexiac,d | 19 | 0.4 | 11 | 2
BCVA = best‑corrected visual acuity; BVd = BLENREP + bortezomib and dexamethasone; DVd = daratumumab + bortezomib and dexamethasone.
a Adverse reactions, except ophthalmic exam findings, were graded according to Common Terminology Criteria for Adverse Events v5.0.
b Based on ophthalmic exam findings.
c Grouped term includes other related terms.
d Includes the following fatal adverse reactions: BVd: pneumonia (n = 10), COVID-19 (n = 3), upper respiratory tract infection (n = 1); DVd: pneumonia (n = 7), COVID-19 (n = 5), pyrexia (n = 1).

Clinically relevant adverse reactions in <10% of patients who received BVd included: increased lacrimation, vomiting, diplopia, albuminuria, sepsis, eye pruritus, infusion-related reactions, corneal ulcer (including cases with infection), and pneumonitis.

Table 5 summarizes the laboratory abnormalities in DREAMM-7.

Table 5. Select Laboratory Abnormalities (>10%) That Worsened from Baseline in Patients with Relapsed or Refractory Multiple Myeloma Who Received BLENREP in DREAMM-7
Laboratory Abnormality | BLENREP + Bortezomib and Dexamethasonea |  | Daratumumab + Bortezomib and Dexamethasonea
Laboratory Abnormality | All Grades (%) | Grades 3‑4 (%) | All Grades (%) | Grades 3‑4 (%)
Hematology
Platelets decreased | 100 | 74 | 88 | 48
Lymphocytes decreased | 90 | 53 | 92 | 56
Leukocytes decreased | 59 | 11 | 67 | 17
Neutrophils decreased | 52 | 17 | 53 | 13
Hemoglobin decreased | 51 | 10 | 60 | 12
Chemistry
Aspartate aminotransferase increased | 88 | 5 | 40 | 0
Gamma glutamyltransferase increased | 73 | 15 | 44 | 3
Alanine aminotransferase increased | 71 | 5 | 54 | 1
Creatinine increased | 51 | 2 | 53 | <1
Creatine phosphokinase increased | 48 | 3 | 31 | 3
BVd = BLENREP + bortezomib and dexamethasone; DVd = daratumumab + bortezomib and dexamethasone.
a The denominator used to calculate the rate varied from 238 to 241 (BVd) and 243 to 246 (DVd) based on the number of patients with a baseline value and at least one post-treatment value.

Patient-reported ocular symptoms were assessed using the Patient-Reported Outcomes Common Terminology Criteria for Adverse Events (PRO-CTCAE) and Ocular Surface Disease Index (OSDI).

PRO-CTCAE assessments were collected at baseline and then every 3 weeks until treatment discontinuation. Completion rates in both arms were ≥90% at baseline and ≥81% at subsequent timepoints where >50% of patients remained on treatment. OSDI assessments were collected every 3 weeks until the 6th dose and then every 6 weeks thereafter until treatment discontinuation for BVd and every 3 weeks until Cycle 6 and then every 12 weeks thereafter until treatment discontinuation for DVd. Completion rates in both arms were ≥90% at baseline and ≥52% at subsequent timepoints where >50% of patients remained on treatment.

Table 6 summarizes the patient-reported symptom of blurred vision as assessed by PRO-CTCAE.

Table 6. Patient-Reported Symptom of Blurred Vision Assessed by PRO-CTCAE in Patients with Relapsed or Refractory Multiple Myeloma in DREAMM-7
Symptom (Attribute)a | Any Symptom Before Treatmentb |  | Score 3 or 4 Before Treatmentc |  | Any Symptom on Treatmentd,e |  | Score 3 or 4 on Treatmentd,f
Symptom (Attribute)a | BVd (%) n = 232 | DVd (%) n = 227 | BVd (%) n = 232 | DVd (%) n = 227 | BVd (%) n = 238 | DVd (%) n = 239 | BVd (%) n = 238 | DVd (%) n = 239
Blurred vision (severity) | 28 | 24 | <1 | 2 | 93 | 74 | 55 | 15
BVd = BLENREP + bortezomib and dexamethasone; DVd = daratumumab + bortezomib and dexamethasone; PRO-CTCAE = patient-reported outcomes common terminology criteria for adverse events.
a Symptom attribute scoring defined as severity with a score of 0 = ‘none’; 1 = ‘mild’; 2 = ‘moderate’; 3 = ‘severe’; 4 = ‘very severe’.
b Percentage of patients whose symptom score before treatment was 1 to 4.
c Percentage of patients whose symptom score before treatment was 3 or 4.
d Number of patients who provided at least one on-treatment score.
e Percentage of patients whose maximum post-baseline score was 1 to 4 on treatment.
f Percentage of patients whose maximum post-baseline score was 3 or 4 on treatment.

Driving at night was assessed using the OSDI. At baseline, the proportion of patients who reported limitations with driving at night “all of the time” or “most of the time” during the last week was 9% in the BVd arm and 4% in the DVd arm. The proportion of patients who reported limitations with driving at night “all of the time” or “most of the time” during the last week was highest in the BVd arm at 47% at Week 13 and in the DVd arm at 12% at Week 76.

8 USE IN SPECIFIC POPULATIONS

8.1 Pregnancy

Risk Summary

Based on its mechanism of action, BLENREP can cause fetal harm when administered to a pregnant woman, because it contains a genotoxic compound (the microtubule inhibitor, MMAF) and it targets actively dividing cells [see Clinical Pharmacology (12.1), Nonclinical Toxicology (13.1)]. Human immunoglobulin G (IgG) is known to cross the placenta; therefore, belantamab mafodotin-blmf has the potential to be transmitted from the mother to the developing fetus. There are no available data on the use of BLENREP in pregnant women to evaluate for drug-associated risk. No animal reproduction studies were conducted with BLENREP. Advise pregnant women of the potential risk to a fetus.

In the U.S. general population, the estimated background risk of major birth defects and miscarriage in clinically recognized pregnancies is 2% to 4% and 15% to 20%, respectively.

Data

Animal Data: Animal reproductive or developmental toxicity studies were not conducted with belantamab mafodotin‑blmf. The cytotoxic component of BLENREP, mcMMAF, disrupts microtubule function, is genotoxic, and can be toxic to rapidly dividing cells, suggesting it has the potential to cause embryo‑fetal toxicity.

8.2 Lactation

Risk Summary

There are no data on the presence of belantamab mafodotin-blmf in human milk or the effects on the breastfed child or milk production. Because of the potential for serious adverse reactions in the breastfed child, advise women not to breastfeed during treatment with BLENREP and for 3 months after the last dose.

8.3 Females and Males of Reproductive Potential

BLENREP can cause fetal harm when administered to pregnant women [see Use in Specific Populations (8.1)].

Pregnancy Testing

Verify the pregnancy status of females of reproductive potential prior to initiating BLENREP.

Contraception

Females: Advise females of reproductive potential to use effective contraception during BLENREP treatment and for 4 months after the last dose.

Males: Because of the potential for genotoxicity, advise males with female partners of reproductive potential to use effective contraception during treatment with BLENREP and for 6 months after the last dose [see Nonclinical Toxicology (13.1)].

Infertility

Based on findings in animal studies, BLENREP may impair fertility in females and males. The effects were not reversible in male rats but were reversible in female rats [see Nonclinical Toxicology (13.1)].

8.4 Pediatric Use

The safety and effectiveness of BLENREP in pediatric patients have not been established.

8.5 Geriatric Use

Of 242 patients who received BLENREP in DREAMM-7, 121 patients (50%) were aged 65 years or older and 37 patients (15%) were 75 years or older. No overall differences in the safety of BLENREP were observed between patients 65 years of age and older and younger adult patients.

Of the 108 patients who received BLENREP and were evaluated for efficacy in the DREAMM-7 study, there was an insufficient number of older adult patients to determine if the effectiveness in patients 65 years of age and older is different than in younger adult patients.

8.6 Hepatic Impairment

No dose adjustment is recommended for patients with mild hepatic impairment (total bilirubin > upper limit of normal [ULN] to ≤1.5 × ULN and any aspartate aminotransferase [AST] or total bilirubin ≤ULN with AST >ULN).

The recommended dose of BLENREP has not been established in patients with moderate or severe hepatic impairment [see Clinical Pharmacology (12.3)].

11 DESCRIPTION

Belantamab mafodotin‑blmf is a B‑cell maturation antigen (BCMA)‑directed antibody and microtubule inhibitor conjugate. Belantamab mafodotin‑blmf is an antibody conjugate composed of 3 components: 1) afucosylated, humanized immunoglobulin G1 monoclonal antibody covalently linked to 2) the microtubule inhibitor mcMMAF via 3) a protease‑resistant maleimidocaproyl linker.

The antibody is produced in a mammalian cell line (Chinese Hamster Ovary) using recombinant DNA technology and the microtubule inhibitor and linker are produced by chemical synthesis. Approximately 4 molecules of mafodotin are attached to each antibody molecule. The molecular weight of belantamab mafodotin‑blmf is approximately 152 kDa. Belantamab mafodotin‑blmf has the following structure:

BLENREP (belantamab mafodotin‑blmf) for injection is a sterile, preservative‑free, white to yellow, lyophilized powder in a single‑dose vial for reconstitution and further dilution prior to intravenous use. BLENREP is supplied as 70 mg per vial and requires reconstitution with 1.4 mL of Sterile Water for Injection, USP, to obtain a concentration of 50 mg/mL. Each mL of reconstituted solution contains belantamab mafodotin‑blmf (50 mg) and the inactive ingredients, citric acid monohydrate (0.46 mg), edetate disodium (0.017 mg), polysorbate 80 (0.2 mg), sodium citrate (5.88 mg), and trehalose (68.4 mg). The pH of the reconstituted solution is 6.2.

12 CLINICAL PHARMACOLOGY

12.1 Mechanism of Action

Belantamab mafodotin‑blmf is an antibody‑drug conjugate (ADC). The antibody component is an afucosylated IgG1 directed against BCMA, a protein expressed on normal B lymphocytes and multiple myeloma cells. The small molecule component is mcMMAF, a microtubule inhibitor. Upon binding to BCMA, belantamab mafodotin‑blmf is internalized followed by release of the cytotoxic agent (cys‑mcMMAF) via proteolytic cleavage. The released cys‑mcMMAF intracellularly disrupts the microtubule network, leading to cell cycle arrest and apoptosis.

Belantamab mafodotin‑blmf had antitumor activity in multiple myeloma cells and mediated killing of tumor cells through cys‑mcMMAF‑induced apoptosis, as well as by tumor cell lysis through antibody‑dependent cellular cytotoxicity and antibody‑dependent cellular phagocytosis.

12.2 Pharmacodynamics

Exposure‑Response Relationships

When BLENREP was used in combination with Vd, higher belantamab mafodotin‑blmf Cycle 1 exposure was associated with a higher incidence of some safety adverse reactions (e.g., Grade ≥2 corneal exam findings).

Cardiac Electrophysiology

Belantamab mafodotin‑blmf had no meaningful QTc prolongation (>10 ms) at the recommended dosage.

12.3 Pharmacokinetics

Belantamab mafodotin‑blmf exhibited dose‑proportional pharmacokinetics, with a gradual decrease in clearance over time. After a planned infusion duration of 30 minutes, maximum belantamab mafodotin‑blmf plasma concentrations occurred at or shortly after the end of the infusion. Accumulation of belantamab mafodotin‑blmf was minimal to moderate for the ADC (Cycle 3 to Cycle 1 ratio was 1.13 for Cmax and 1.58 for AUC) as observed with a dosing regimen of every 3 weeks.

Table 7 describes the pharmacokinetics of belantamab mafodotin‑blmf for the 2.5 mg/kg dose on Cycle 1 at the end of the first 3‑week intervals.

Table 7. Summary of Pharmacokinetic Parametersa
 | AUCb | Cmax | Ctau
ADC; (%) | 3,950 mcg•h/mL; (30.6) | 43.7 mcg/mL; (22.1) | 2.03 mcg/mL; (62.5)
cys‑mcMMAF; (%) | 94.2 ng•h/mL; (42.3) | 0.976 ng/mL; (45.3) | –
ADC = antibody drug conjugate; AUC = area under the curve; Cmax = maximum plasma concentration; Ctau = concentration at the end of a dosing interval.
a Data presented as geometric mean (CV%).
b AUC for ADC is AUC(0‑21days) and for cys-mcMMAF is AUC(0‑7days).

Distribution

In vitro, cys‑mcMMAF exhibited low protein binding (70% unbound at a concentration of 5 ng/mL) in human plasma.

The geometric mean (CV%) steady‑state volume of distribution of belantamab mafodotin‑blmf was 10.8 L (22.2%).

Elimination

The geometric mean (CV%) belantamab mafodotin‑blmf (ADC) initial systemic clearance (CL) was 0.901 L/day (40%), and the elimination half‑life was 13 days (26%). Following treatment, steady‑state CL was 0.605 L/day (43%) or approximately 33% lower than initial systemic CL with an elimination half‑life of 17 days (31%).

The fraction of intact cys‑mcMMAF excreted in urine was approximately 18% of the dose in Cycle 1, with no evidence of other mcMMAF‑related metabolites.

Metabolism: The monoclonal antibody portion of belantamab mafodotin‑blmf is expected to undergo proteolysis to small peptides and individual amino acids by ubiquitous proteolytic enzymes. Cys‑mcMMAF had limited metabolic clearance in human hepatic S9 fraction incubation studies.

Specific Populations

No clinically significant differences in the pharmacokinetics of belantamab mafodotin‑blmf were observed based on age (32 to 89 years), sex, race (White vs. Black vs. Asian), body weight (37 to 170 kg), mild to severe renal impairment and kidney failure (eGFR <30 mL/min), or mild hepatic impairment (total bilirubin >ULN to ≤1.5 × ULN and any AST or total bilirubin ≤ULN with AST >ULN).

The effects of moderate (total bilirubin >1.5 × ULN to ≤3 × ULN and any AST) or severe hepatic impairment (total bilirubin >3 × ULN and any AST) on the pharmacokinetics of belantamab mafodotin‑blmf are unknown.

In Vitro Studies:

Cytochrome P450 (CYP) Enzymes: Cys-mcMMAF is not an inhibitor, an inducer, or a sensitive substrate of cytochrome P450 enzymes.

Transporter Systems: Cys‑mcMMAF is a substrate of organic anion transporting polypeptide (OATP)1B1 and OATP1B3, multidrug resistance‑associated protein (MRP)1, MRP2, and MRP3, bile salt export pump (BSEP), and a possible substrate of P‑glycoprotein (P‑gp).

12.6 Immunogenicity

The observed incidence of anti‑drug antibodies is highly dependent on the sensitivity and specificity of the assay. Differences in assay methods preclude meaningful comparisons of the incidence of anti‑drug antibodies in the studies described below with the incidence of anti‑drug antibodies (ADAs) in other studies, including those of BLENREP or of other belantamab mafodotin‑blmf products.

In the combination therapy studies, 3% of patients (15/515) tested positive for treatment‑emergent belantamab mafodotin‑blmf ADAs. Among the 15 patients who tested positive for ADAs, 2 patients tested positive for neutralizing anti‑belantamab mafodotin‑blmf antibodies.

13 NONCLINICAL TOXICOLOGY

13.1 Carcinogenesis, Mutagenesis, Impairment of Fertility

Carcinogenicity studies have not been conducted with belantamab mafodotin‑blmf.

Belantamab mafodotin‑blmf was genotoxic in an in vitro micronucleus assay in human lymphocytes through an aneugenic mechanism. These results are consistent with the pharmacological effect of MMAF binding to tubulin causing microtubule depolymerization resulting in spindle disorganization during cell division. Cys‑mcMMAF was not mutagenic in the bacterial reverse mutation assay (Ames test), the L5178Y mouse lymphoma forward mutation assay, or the in vivo rat bone marrow micronucleus assay.

Fertility studies have not been conducted with belantamab mafodotin‑blmf. Results of repeat‑dose toxicity studies with intravenous administration of belantamab mafodotin‑blmf in rats indicate the potential for impaired male and female reproductive function and fertility. In rats, weekly dosing for 3 weeks at doses ≥10 mg/kg (approximately 5 times the exposure at the maximum recommended human dose [MRHD] of 2.5 mg/kg based on AUC) resulted in degeneration and atrophy of seminiferous tubules in the testes and luteinized nonovulatory follicles in the ovaries. Findings in females were reversible; findings in the testes were not reversible at the end of the 12‑week recovery period with weekly dosing or when given every 3 weeks for 13 weeks at doses ≥10 mg/kg. In male monkeys, the highest dose tested of 10 mg/kg (approximately 5 times the exposure at the MRHD based on AUC) given weekly for 13 weeks resulted in seminiferous tubules degeneration in the testes that was fully reversed following the 12‑week recovery period.

14 CLINICAL STUDIES

Relapsed or Refractory Multiple Myeloma in Combination with Bortezomib and Dexamethasone

The efficacy of BLENREP in combination with bortezomib and dexamethasone (BVd) compared with daratumumab, bortezomib, and dexamethasone (DVd) was evaluated in DREAMM‑7 (NCT04246047), an open‑label, randomized, multicenter study in adult patients with relapsed or refractory multiple myeloma. Patients received at least one prior line of therapy and had documented disease progression during or after their most recent line of treatment. Patients who were refractory or intolerant to daratumumab or bortezomib, or with prior exposure to anti‑BCMA therapy were excluded. Patients with existing corneal disease, except for mild punctate keratopathy, were excluded.

Patients were randomized 1:1 to the following treatment arms:

- BLENREP 2.5 mg/kg (IV) every 3 weeks on Day 1 of each 21‑day cycle. Bortezomib 1.3 mg/m^2 (subcutaneously) on Days 1, 4, 8, and 11 and dexamethasone 20 mg (IV or orally) on the day of, and the day after, bortezomib treatment of Cycles 1–8 (21‑day cycles). From Cycle 9 onward, treatment with BLENREP was continued as a single agent.
- Daratumumab 16 mg/kg (IV) every week for Cycles 1–3 and every 3 weeks for Cycles 4–8. Bortezomib 1.3 mg/m^2 (subcutaneously) on Days 1, 4, 8, and 11 and dexamethasone 20 mg (IV or orally) on the day of, and the day after, bortezomib treatment of Cycles 1–8 (21‑day cycles). From Cycle 9 onward, treatment with daratumumab was continued as a single agent.

The dose level of dexamethasone in each arm was reduced by half in patients aged 75 years or older. Treatment with BLENREP or daratumumab was continued until disease progression or unacceptable toxicity.

Efficacy was established based on progression-free survival (PFS) and overall survival (OS).

A total of 217 patients who received at least two prior lines of therapy, including a proteasome inhibitor and immunomodulatory agent, were evaluated for efficacy: 108 in the BVd arm and 109 in the DVd arm. Baseline demographics and characteristics were similar across arms. The median age was 65 years (range: 39 to 86); 43% were age 65 to 74 years, 11% age 75 years or older; 53% were male; 86% were White, 11% Asian, 2% Black; R-ISS stage at screening was stage I in 37%, stage II in 56%, stage III in 6%; high‑risk cytogenetics (presence of t (11;14), t (14;16) or 17p13del) were present in 29%; extramedullary disease was present in 11%. The median number of prior lines of therapy was 3 (range: 2 to 7); 2% received a prior anti-CD38 monoclonal antibody, and 71% previously received autologous stem cell transplantation. Overall, 19% of patients were refractory to proteasome inhibitors and 59% were refractory to immunomodulatory agents.

Efficacy results are summarized in Table 8 and Figures 1 and 2.

Table 8. Efficacy Results from DREAMM-7
 | BLENREP + Bortezomib and Dexamethasone N = 108 | Daratumumab + Bortezomib and Dexamethasone N = 109
Progression‑Free Survival (PFS)a,b,c
Number (%) of patients with event | 42 (39) | 73 (67)
Median in months (95% CI)d | 31.3 (23.5, NR) | 10.4 (7, 13.4)
Hazard ratio (95% CI)e | 0.31 (0.21, 0.47)
Overall Survival (OS)a,f
Number (%) of patients with event | 33 (31) | 57 (52)
Median in months (95% CI)d | NR (NR, NR) | 35.7 (21.1, NR)
Hazard ratio (95% CI)e | 0.49 (0.32, 0.76)
Overall Response Rate (ORR)a,b,c,g, %; (95% CI) | 81.5; (72.9, 88.3) | 56.9; (47, 66.3)
Stringent complete response (sCR), n (%) | 15 (13.9) | 4 (3.7)
Complete response (CR), n (%) | 19 (17.6) | 5 (4.6)
Very good partial response (VGPR), n (%) | 34 (31.5) | 23 (21.1)
Partial response (PR), n (%) | 20 (18.5) | 30 (27.5)
Minimal Residual Disease (MRD) Negativity Ratea,b,h, n (%) | 25 (23.1) | 3 (2.8)
95% CI | (15.6, 32.2) | (0.6, 7.8)
MRD Negativity Rate in Patients with CR or Betterb,h
Number of patients with CR or better | 34 | 9
MRD negativity rate, n (%) | 25 (73.5) | 3 (33.3)
(95% CI) | (55.6, 87.1) | (7.5, 70.1)
NR = not reached.
a Based on all randomized patients who received at least two prior lines of therapy, including a proteasome inhibitor and immunomodulatory agent.
b Median follow-up of 27.9 months.
c Response was based on Independent Review Committee per International Myeloma Working Group criteria.
d By Brookmeyer and Crowley method.
e Based on stratified Cox regression model.
f Median follow-up of 38.7 months.
g ORR: sCR+CR+VGPR+PR.
h Assessed by next generation sequencing assay (clonoSEQ) at 10^‑5 threshold.

Figure 1: Kaplan-Meier Curve for Progression‑Free Survival in DREAMM-7

Figure 2: Kaplan-Meier Curve for Overall Survival in DREAMM-7

In patients who achieved response, the median time to response was 1.43 months (range: 0.7 to 8.4 months) in the BVd arm and 1.03 months (range: 0.7 to 11.1 months) in the DVd arm.

15 REFERENCES

1. “OSHA Hazardous Drugs.” OSHA. http://www.osha.gov/SLTC/hazardousdrugs/index.html.

16 HOW SUPPLIED/STORAGE AND HANDLING

BLENREP (belantamab mafodotin‑blmf) for injection is a sterile, preservative‑free, white to yellow lyophilized powder for reconstitution and further dilution prior to intravenous use.

BLENREP is supplied in a carton containing one 70 mg single‑dose vial with a rubber stopper (not made with natural rubber latex) and aluminum overseal with removable cap (NDC 0173‑0913‑01).

Store vials refrigerated at 36ºF to 46ºF (2ºC to 8ºC).

BLENREP is a hazardous drug. Follow applicable special handling and disposal procedures.^1

17 PATIENT COUNSELING INFORMATION

Advise the patient to read the FDA‑approved patient labeling (Medication Guide).

Ocular Toxicity

- Advise patients that ocular toxicity may occur during treatment with BLENREP [see Warnings and Precautions (5.1)].
- Advise patients to promptly tell their healthcare provider if they notice any new or worsening eye symptoms [see Dosage and Administration (2.1), Warnings and Precautions (5.1)].
- Advise patients that they will be sent to an eye care professional to obtain ophthalmic exams before starting BLENREP, before each dose, promptly for any new or worsening eye symptoms, and as clinically indicated [see Dosage and Administration (2.1), Warnings and Precautions (5.1)].
- Advise patients to administer preservative‑free artificial tears at least 4 times per day starting with the first infusion and continuing until the end of treatment and to avoid wearing contact lenses for the duration of therapy. Bandage contact lenses may be used under the direction of an eye care professional [see Dosage and Administration (2.1, 2.3), Warnings and Precautions (5.1)].
- Advise patients to use caution when driving or operating machinery as BLENREP may adversely affect their vision [see Warnings and Precautions (5.1)].

BLENREP REMS

- Advise patients that because of the risk of ocular toxicity, BLENREP is available only through a restricted program called the BLENREP REMS [see Warnings and Precautions (5.2)].
- Patients must receive counseling about the risk of ocular toxicity, enroll in the REMS, and adhere to ongoing monitoring via ophthalmic exams. Patients will be given the BLENREP REMS Patient Guide. This guide describes the risk of ocular toxicity with BLENREP [see Warnings and Precautions (5.2)].

Thrombocytopenia

- Advise patients to inform their healthcare provider if they develop signs or symptoms of bleeding [see Warnings and Precautions (5.3)].

Embryo‑fetal Toxicity

- Advise pregnant women of the potential risk to a fetus. Advise females of reproductive potential to inform their healthcare provider of a known or suspected pregnancy [see Warnings and Precautions (5.4), Use in Specific Populations (8.1, 8.3)].
- Advise females of reproductive potential to use effective contraception during treatment with BLENREP and for 4 months after the last dose [see Warnings and Precautions (5.4), Use in Specific Populations (8.3)].
- Advise males with female partners of reproductive potential to use effective contraception during treatment with BLENREP and for 6 months after the last dose [see Use in Specific Populations (8.3), Nonclinical Toxicology (13.1)].

Lactation

- Advise women not to breastfeed during treatment with BLENREP and for 3 months after the last dose [see Use in Specific Populations (8.2)].

Infertility

- Advise males and females of reproductive potential that BLENREP may impair fertility [see Use in Specific Populations (8.3)].

Pneumonitis

- Advise patients to immediately report any new or worsening respiratory symptoms to their healthcare provider [see Adverse Reactions (6.1)].

Trademarks are owned by or licensed to the GSK group of companies.

Manufactured by:
GlaxoSmithKline LLC
Philadelphia PA, 19104
U.S. License No. 1727

For:
GlaxoSmithKline
Durham, NC 27701
©2025 GSK group of companies or its licensor.
BLP:1PI

MEDICATION GUIDE

BLENREP (BLEN-REP)

(belantamab mafodotin-blmf)

for injection, for intravenous use

What is the most important information I should know about BLENREP?

BLENREP can cause serious side effects, including:

- Eye problems. Eye problems are common with BLENREP and can also be severe. BLENREP can cause changes to the surface of your eye, which can lead to symptoms of eye problems, including:

- decreased vision
- blurred vision
- dry eyes
- sensitivity to light

- feeling like something is in your eyes
- eye irritation
- eye pain

Ulcers on the surface of the eye (corneal ulcers), including with infection, may also happen during treatment with BLENREP.

Tell your healthcare provider right away if you notice any new or worsening eye symptoms or vision changes during treatment with BLENREP.

Your healthcare provider will refer you to an eye care specialist (such as an ophthalmologist or optometrist) to check your eyes before you start treatment, before you receive each dose of BLENREP, and as needed for any new or worsening eye problems. It is important that you:

  - Keep all of your eye care appointments because some changes can happen without symptoms and may only be seen on an eye exam.
  - Use preservative‑free artificial tears at least 4 times per day starting with your first infusion and continuing until the end of treatment with BLENREP.
  - Avoid wearing contact lenses during treatment with BLENREP unless directed by your eye care specialist.
  - Use caution when driving or operating machinery because BLENREP may cause changes to your vision.

Because of the risk of eye problems, BLENREP is available only through a restricted program called the BLENREP Risk Evaluation and Mitigation Strategy (REMS). Your healthcare provider will give you the BLENREP REMS Patient Guide, which describes the risk of eye problems, and will explain the REMS program to you. To receive BLENREP, you must enroll in the REMS program and receive eye exams during treatment. See “What are the possible side effects of BLENREP?” for more information about side effects.

What is BLENREP?

BLENREP is a prescription medicine used in combination with the medicines bortezomib and dexamethasone to treat adults with multiple myeloma who:

- have received at least 2 prior treatments, including a proteasome inhibitor and an immunomodulatory agent, and
- their cancer has come back or did not respond to prior treatment.

It is not known if BLENREP is safe and effective in children.

Before receiving BLENREP, tell your healthcare provider about all of your medical conditions, including if you:

- have or had vision or eye problems.
- have or had bleeding problems.
- are pregnant or plan to become pregnant. BLENREP can harm your unborn baby.
  Females who are able to become pregnant:
  - Your healthcare provider will do a pregnancy test before you start treatment with BLENREP.
  - Use effective birth control during treatment with BLENREP and for 4 months after the last dose. Talk to your healthcare provider about birth control methods you can use during this time.
  - Tell your healthcare provider if you become pregnant or think you may be pregnant during treatment with BLENREP.
Males with female partners who are able to become pregnant:
  1. Use effective birth control during treatment with BLENREP and for 6 months after the last dose.
- are breastfeeding or plan to breastfeed. It is not known if BLENREP passes into your breast milk. Do not breastfeed during treatment with BLENREP and for 3 months after the last dose.

Tell your healthcare provider about all the medicines you take, including prescription and over‑the‑counter medicines, vitamins, and herbal supplements.

How will I receive BLENREP?

- Your healthcare provider will give you BLENREP as an infusion into your vein over about 30 minutes.
- BLENREP is usually given every 3 weeks.
- Your healthcare provider will decide how many treatments you will need.
- If you miss any appointments, call your healthcare provider as soon as possible to reschedule your appointment.

What are the possible side effects of BLENREP?

BLENREP can cause serious side effects, including:

- See “Eye Problems” in “What is the most important information I should know about BLENREP?”
- Decrease in platelets (thrombocytopenia) is common with BLENREP and can also be severe. Platelets are a type of blood cell that help your blood to clot. Your healthcare provider will check your blood cell counts before you start treatment with BLENREP and during treatment as needed. Tell your healthcare provider if you get any bleeding or bruising during treatment with BLENREP.

The most common side effects of BLENREP when given with bortezomib and dexamethasone include:

- See “Eye problems” in “What is the most important information I should know about BLENREP?”
- upper respiratory tract infection
- liver problems
- diarrhea

- tiredness
- pneumonia
- cataract
- COVID-19

The most common severe abnormal blood test results during treatment with BLENREP include decreases in platelets, white blood cells, and hemoglobin, and increases in certain liver enzymes.

Tell your healthcare provider right away if you get new or worsening unexplained signs or symptoms of lung problems, including shortness of breath, chest pain, or cough.

Your healthcare provider may decrease your dose, temporarily stop, or completely stop treatment with BLENREP if you get serious side effects.

BLENREP may affect fertility in males and females, which may affect your ability to have children. Talk to your healthcare provider if this is a concern for you.

These are not all of the possible side effects of BLENREP.

Call your doctor for medical advice about side effects. You may report side effects to FDA at 1‑800‑FDA‑1088.

General information about the safe and effective use of BLENREP.

Medicines are sometimes prescribed for purposes other than those listed in a Medication Guide. You can ask your pharmacist or healthcare provider for information about BLENREP that is written for health professionals.

What are the ingredients in BLENREP?

Active Ingredient: belantamab mafodotin-blmf

Inactive Ingredients: citric acid monohydrate, edetate disodium, polysorbate 80, sodium citrate, and trehalose.

Manufactured by:

GlaxoSmithKline LLC

Philadelphia PA, 19104

U.S. License No. 1727

For:

GlaxoSmithKline, Durham, NC 27701

©2025 GSK group of companies or its licensor.

BLP:1MG

For more information, call GlaxoSmithKline (GSK) at 1‑888‑825‑5249.

Trademarks are owned by or licensed to the GSK group of companies.

This Medication Guide has been approved by the U.S. Food and Drug Administration. Revised: 10/2025

PACKAGE LABEL

NDC 0173-0913-01

BLENREP

(belantamab mafodotin-blmf)

for injection

70 mg/vial

Rx Only

For intravenous infusion after reconstitution and dilution.

CAUTION: Hazardous Drug.

No preservative.

Dispense the enclosed Medication Guide to each patient.

Contains one Single-Dose vial.

Discard Unused Portion.

2025 GSK group of companies or its licensor.

Product Italy

Rev. 04/25

62000000097965